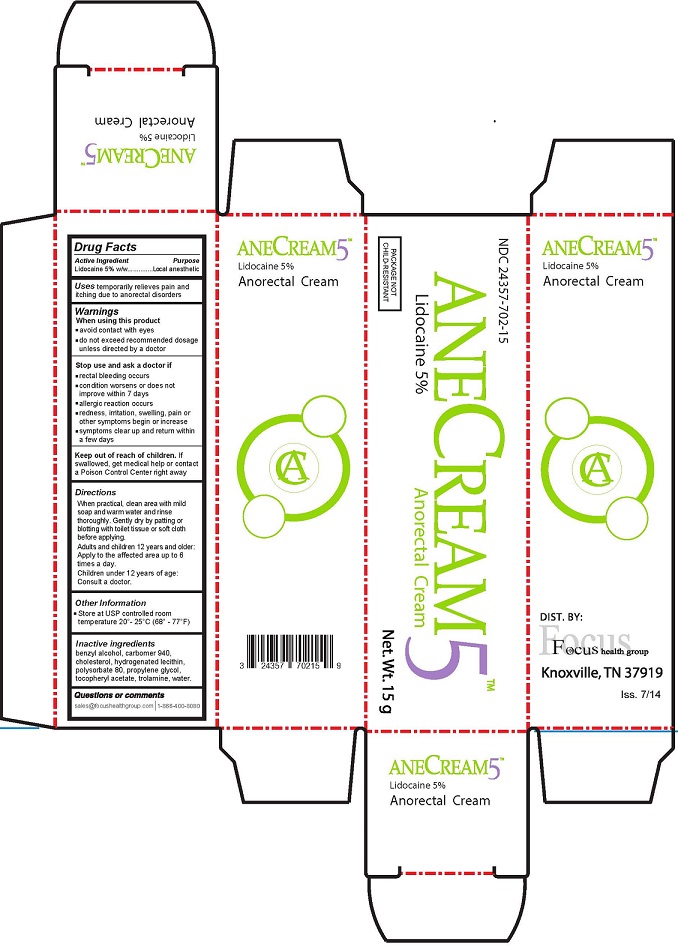 DRUG LABEL: Anecream 5
NDC: 24357-702 | Form: CREAM
Manufacturer: Focus Health Group
Category: otc | Type: HUMAN OTC DRUG LABEL
Date: 20250115

ACTIVE INGREDIENTS: LIDOCAINE 5 g/100 g
INACTIVE INGREDIENTS: BENZYL ALCOHOL; CARBOMER HOMOPOLYMER TYPE C; CHOLESTEROL; LECITHIN, SOYBEAN; POLYSORBATE 80; PROPYLENE GLYCOL; .ALPHA.-TOCOPHEROL ACETATE, DL-; TROLAMINE; WATER; ISOPROPYL MYRISTATE

Anecream 5%

Active Ingredient:

Lidocaine 5% w/w

Purpose

Local anesthetic

Uses

temporarily relieves pain and itching due to anorectal disorders

Warnings

When using this product

- avoid contact with eyes
- do not exceed recommended dosage unless directed by a doctor

Stop and ask a doctor if

- rectal bleeding occurs
- condition worsens or does not improve within 7 days
- allergic reaction occurs
- redness, irritation, swelling, pain or other symptoms begin or increase
- symptoms clear up and return within a few days

Keep out of reach of children.

If swallowed, get medical help or contact a Poison Control Center right away

Directions

- When practical, clean area with mild soap and warm water and rinse thoroughly. Gently dry by patting of blotting with toilet tissue or soft cloth before applying.
- Adults and children 12 years and older: Apply to the affected area up to 6 times a day.
- Children under 12 years of age: Consult a doctor.

Other information

Store at USP controlled room temperature 20-25C (66-77F).

Inactive ingredients

benzyl alcohol, carbomer 940, cholesterol, hydrogenated lecithin, isopropyl myristate, polysorbate 80, propylene glycol, tocopheryl acetate, trolamine, water.

Anecream5 15g Tube Carton

AC 5art 15gm.jpg

The product package shown above represents a sample of that currently in use. Additional packaging may also be available.

Anecream5 Anorectal Cream

Net. Wt. 15g

Distributed by: Focus Health Group

Knoxville, TN 37919

Anecream5 15g Tube Carton